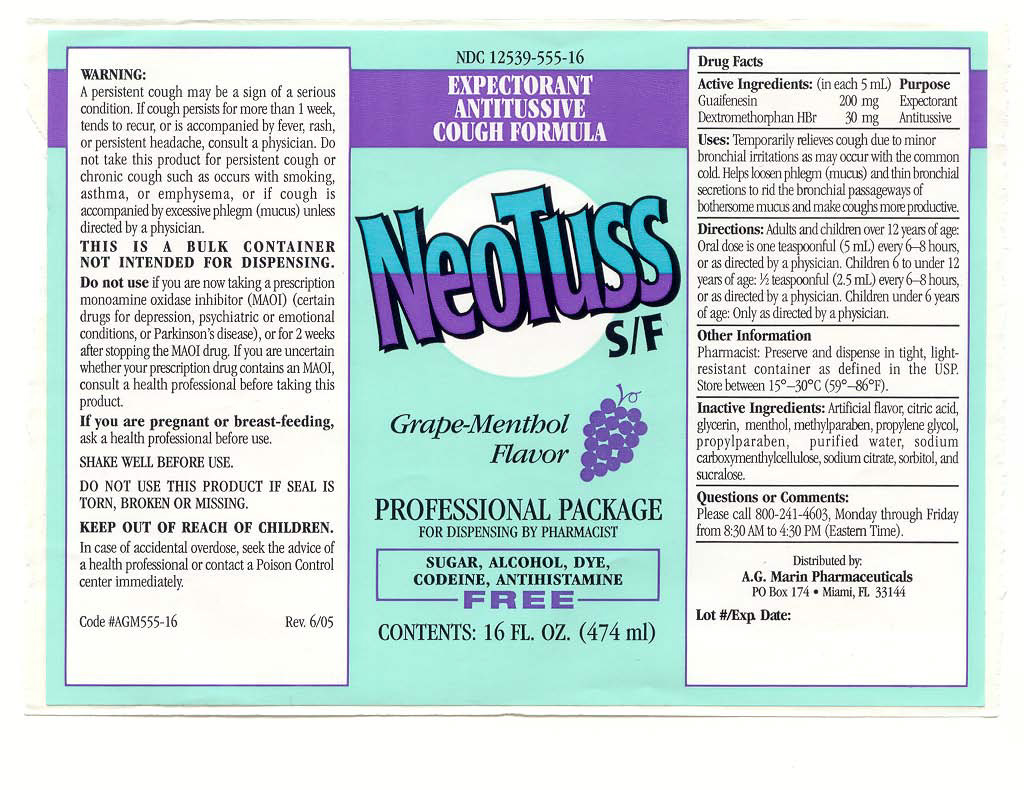 DRUG LABEL: NeoTuss S/F
NDC: 12539-555 | Form: LIQUID
Manufacturer: DORAL PHARMAMEDICS INC dba A.G. Marin Pharmaceuticals
Category: otc | Type: HUMAN OTC DRUG LABEL
Date: 20251218

ACTIVE INGREDIENTS: GUAIFENESIN 200 mg/5 mL; DEXTROMETHORPHAN HYDROBROMIDE 30 mg/5 mL
INACTIVE INGREDIENTS: METHYLPARABEN 7.55 mg/5 mL; PROPYLPARABEN 0.85 mg/5 mL; SUCRALOSE 3.35 mg/5 mL; SORBITOL 1250 mg/5 mL; PROPYLENE GLYCOL 750 mg/5 mL; GLYCERIN 1750 mg/5 mL; HYDROXYETHYLCELLULOSE 2.1 mg/5 mL; MENTHOL 0.4 mg/5 mL; WATER 1023 mg/5 mL

NeoTuss S/F Grape-Menthol Flavor

ACTIVE INGREDIENT

Guaifenesin 200 mg / 5 mL – Purpose: Expectorant

Dextromethorphan HBr 30 mg / 5 mL – Purpose: Antitussive

INACTIVE INGREDIENT

Artificial and natural flavors, glycerin, hydroxyethylcellulose, menthol, methylparaben, propylene glycol, propylparaben, purified water, sorbitol, and sucralose.

INDICATIONS AND USAGE

Temporarily relieves cough due to minor bronchial irritations as may occur with the common cold. Helps loosen phlegm (mucus) and thin bronchial secretions to rid the bronchial passageways of bothersome mucus and make coughs more productive.

Adults and children over 12 years of age: Oral dose in one teaspoonful (5 mL) every 6-8 hours, or as directed by a physician.

Children 6 to under 12 years of age: 1/2 teaspoonful (2.5 mL) every 6-8 hours, or as directed by a physician.

Children under 6 years of age: Only as directed by a physician.

DOSAGE AND ADMINISTRATION

Adults and children over 12 years of age: Oral dose in one teaspoonful (5 mL) every 6-8 hours, or as directed by a physician.

Children 6 to under 12 years of age: 1/2 teaspoonful (2.5 mL) every 6-8 hours, or as directed by a physician.

Children under 6 years of age: Only as directed by a physician.

PURPOSE

Expectorant and Antitussive (cough suppressant)

WHEN USING

Temporarily relieves cough due to minor bronchial irritations as may occur with the common cold. Helps loosen phlegm (mucus) and thin bronchial secretions to rid the bronchial passageways of bothersome mucus and make coughs more productive.

KEEP OUT OF REACH OF CHILDREN

In case of accidental overdose, seek the advice of a health professional or contact a Poison Control Center immediately.

WARNINGS

A persistent cough may be a sign of a serious condition. If cough persists for more than 1 week, tends to recur, or is accompanied by fever, rash, or persistent headache, consult a physician.

Do not take this product for persistent cough or chronic cough such as occurs with smoking, asthma, or emphysema, or if cough is accompanied by excessive phlegm (mucus) unless directed by a physician.

Do not use if you are now taking a prescription monoamine oxidase inhibitor (MAOI) (certain drugs for depression, psychiatric or emotional conditions, or Parkinson’s disease), or for 2 weeks after stopping the MAOI drug.

If you are uncertain whether your prescription drug contains a MAOI, consult a health professional before taking this product.

If pregnant or breast-feeding, ask a health professional before using this product.

OTHER SAFETY INFORMATION

Shake well before use.

Do not use this product if the seal is torn, broken or missing.

Pharmacist: Preserve and dispense in tight, light-resistant containers as defined in the USP.

Store between 15°-30°C (59°-86°F).

Package Label - Principal Display Panel

16 FL. OZ (474 mL) NDC: 12539-555-16